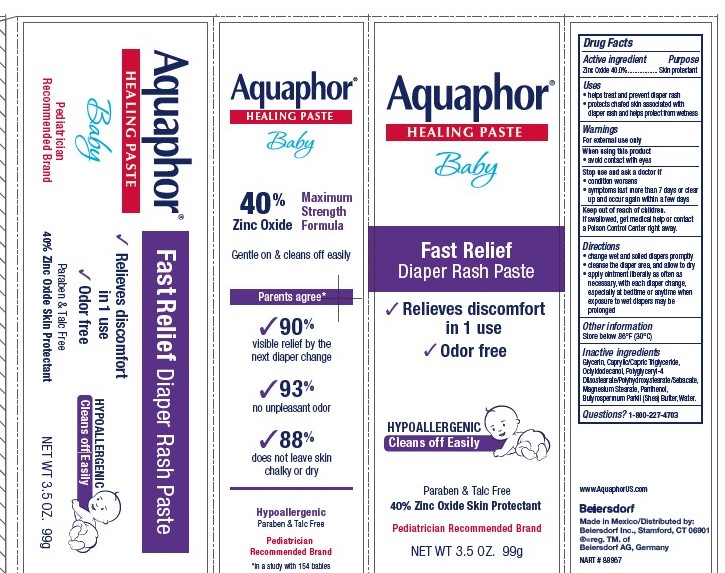 DRUG LABEL: Aquaphor Healing Fast Relief Diaper Rash
NDC: 10356-115 | Form: OINTMENT
Manufacturer: Beiersdorf Inc
Category: otc | Type: HUMAN OTC DRUG LABEL
Date: 20251216

ACTIVE INGREDIENTS: ZINC OXIDE 40 g/100 g
INACTIVE INGREDIENTS: MAGNESIUM STEARATE; PANTHENOL; WATER; OCTYLDODECANOL; MEDIUM-CHAIN TRIGLYCERIDES; POLYGLYCERYL-4 ISOSTEARATE; SHEA BUTTER; GLYCERIN

Aquaphor Healing Fast Relief Diaper Rash Paste

ACTIVE INGREDIENT

Zinc Oxide 40%

PURPOSE

Skin Protectant

Uses
• helps treat and prevent diaper rash
• protects chafed skin associated with diaper rash and helps protect from wetness

Directions
• change wet and soiled diapers promptly • cleanse the diaper area, and allow to dry • apply ointment cream liberally as often as necessary, with each diaper change, especially at bedtime or anytime when exposure to wet diapers may be prolonged

WARNINGS

For external use only

When using this product • avoid contact with eyes

Stop use and ask a doctor if • condition worsens
• symptoms last more than 7 days or clear up and occur
again within a few days

Keep out of reach of children. If swallowed, get medical help
or contact a Poison Control Center right away.

Inactive Ingredients

Glycerin, Caprylic/Capric Triglyceride,

Octyldodecanol, Polyglyceryl-4 Diisostearate/Polyhydroxystearate/Sebacate,

Magnesium Stearate, Panthenol,Butyrospermum Parkii (Shea) Butter, Water

Questions or comments

1-800-227-4703

PACKAGE LABEL

Aquaphor Healing Paste

Baby

Fast Relief Diaper Rash Paste

Relieves Discomfort in 1 Use

Odor free

Hypoallergenic

Cleans off easily

Paraben and Talc Free

40% Zinc Oxide Skin Protectant

Maximum Strength Formula